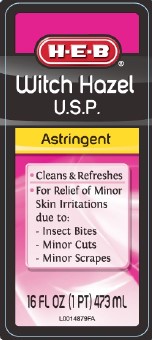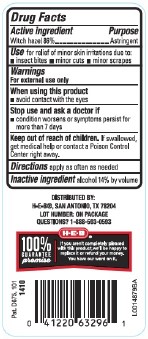 DRUG LABEL: Witch Hazel
NDC: 37808-822 | Form: LIQUID
Manufacturer: H E B
Category: otc | Type: HUMAN OTC DRUG LABEL
Date: 20260224

ACTIVE INGREDIENTS: WITCH HAZEL 860 mg/1 mL
INACTIVE INGREDIENTS: ALCOHOL

HEB 822.001/822AA
Witch Hazel

Active ingredient

Witch Hazel 86%

Purpose

Astringent

Use

for relief of minor skin irritations due to:

- insect bites
- minor cuts
- minor scrapes

Warnings

For external use only

When using this product

avoid contact with the eyes

Stop use and ask a doctor if

- condition worsens or symptoms persist for more than 7 days

Keep out of reach of children.

If swallowed, get medical help or contact a Poison Control Center right away.

Directions

apply as often as needed

Inactive ingredient

alcohol 14% by volume

adverse reaction

DISTRIBUTED BY: H-E-B®, SAN ANTONIO, TX 78204

LOT NUMBER: ON PACKAGE

QUESTIONS? 1-888-593-0593

H-E-B® 100% GUARANTEE promise

If you aren't completely pleased with this product, we'll be happy to replace it or refund your money.

You have our word on it.

Pat. D675, 101

principal display panel

H-E-B®

Witch Hazel U.S.P.

Astringent

- Cleans & Refreshes
- For Relief of Minor Skin Irritations due to - Insects Bites - Minor Cuts - Minor Scrapes

16 FL OZ (1 PTP) 473 mL